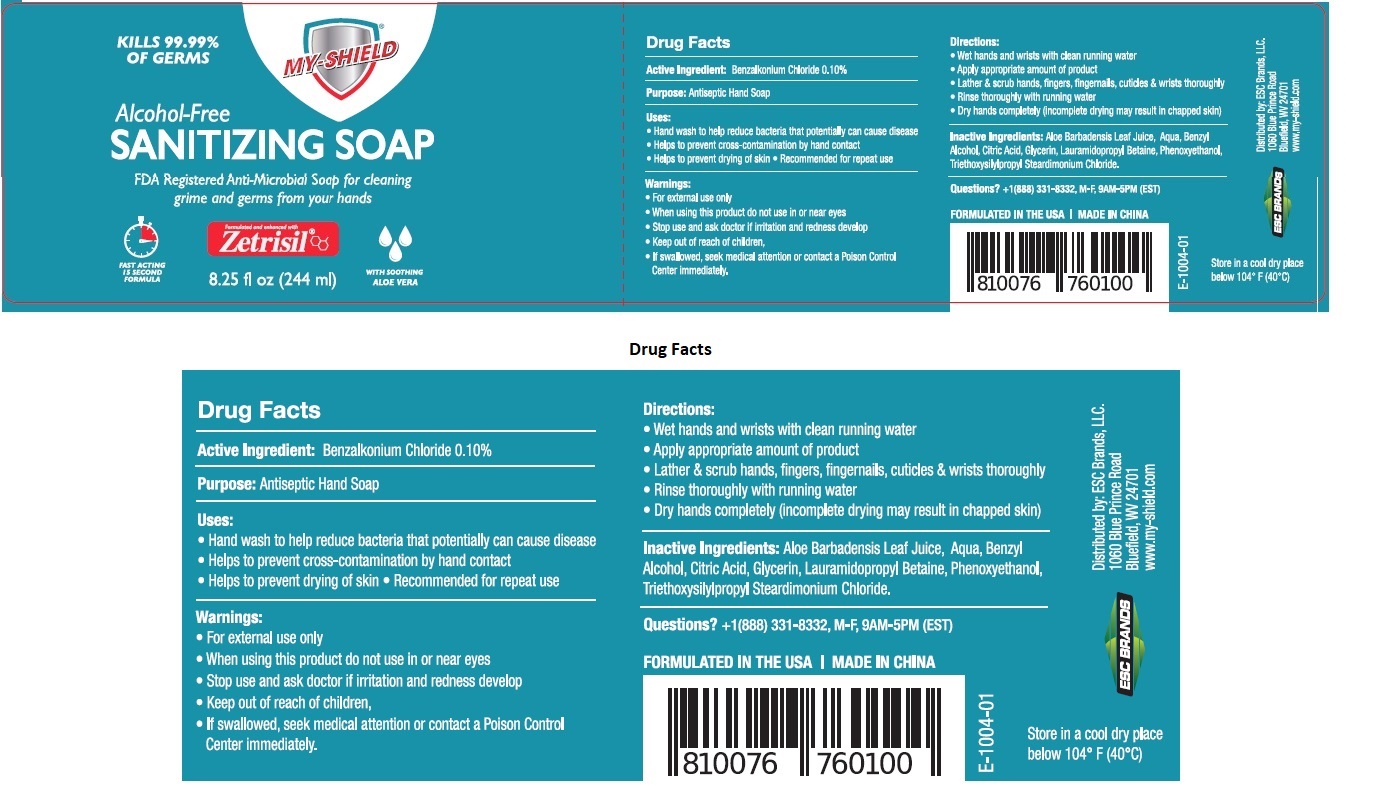 DRUG LABEL: MY-SHIELD SANITIZING
NDC: 71884-040 | Form: SOAP
Manufacturer: Enviro Specialty Chemicals Inc
Category: otc | Type: HUMAN OTC DRUG LABEL
Date: 20241223

ACTIVE INGREDIENTS: BENZALKONIUM CHLORIDE 1 mg/1 mL
INACTIVE INGREDIENTS: ALOE VERA LEAF; WATER; BENZYL ALCOHOL; CITRIC ACID MONOHYDRATE; GLYCERIN; LAURAMIDOPROPYL BETAINE; PHENOXYETHANOL; TRIETHOXYSILYLPROPYL STEARDIMONIUM CHLORIDE

MY-SHIELD SANITIZING SOAP

Active Ingredient:

Benzalkonium Chloride 0.10%

Purpose:

Antiseptic Hand Soap

Uses:

• Hand wash to help reduce bacteria that potentially can cause disease
• Helps to prevent cross-contamination by hand contact
• Helps to prevent drying of skin • Recommended for repeat use

Warnings:

• For external use only
• When using this product do not use in or near eyes
• Stop use and ask doctor if irritation and redness develop

• Keep out of reach of children,
• If swallowed, seek medical attention or contact a Poison Control Center immediately.

Directions:

• Wet hands and wrists with clean running water
• Apply appropriate amount of product
• Lather & scrub hands, fingers, fingernails, cuticles & wrists thoroughly
• Rinse thoroughly with running water
• Dry hands completely (incomplete drying may result in chapped skin)

Inactive Ingredients:

Aloe Barbadensis Leaf Juice, Aqua, Benzyl Alcohol, Citric Acid, Glycerin, Lauramidopropyl Betaine, Phenoxyethanol, Triethoxysilylpropyl Steardimonium Chloride.

Questions?

+1(888) 331-8332, M-F 9AM-5PM (EST)

KILLS 99.99% OF GERMS

Alcohol-Free

FDA Registered Anti-Microbial Soap for cleaning grime and germs from your hands

Formulated and enhanced with Zetrisil®

FAST ACTING 15 SECOND FORMULA

WITH SOOTHING ALOE VERA

FORMULATED IN THE USA | MADE IN CHINA

Store in a cool dry place below 104°F (40°C)

Distributed by: ESC Brands, LLC.

1060 Blue Prince Road

Bluefield, WV 24701

www.my-shield.com